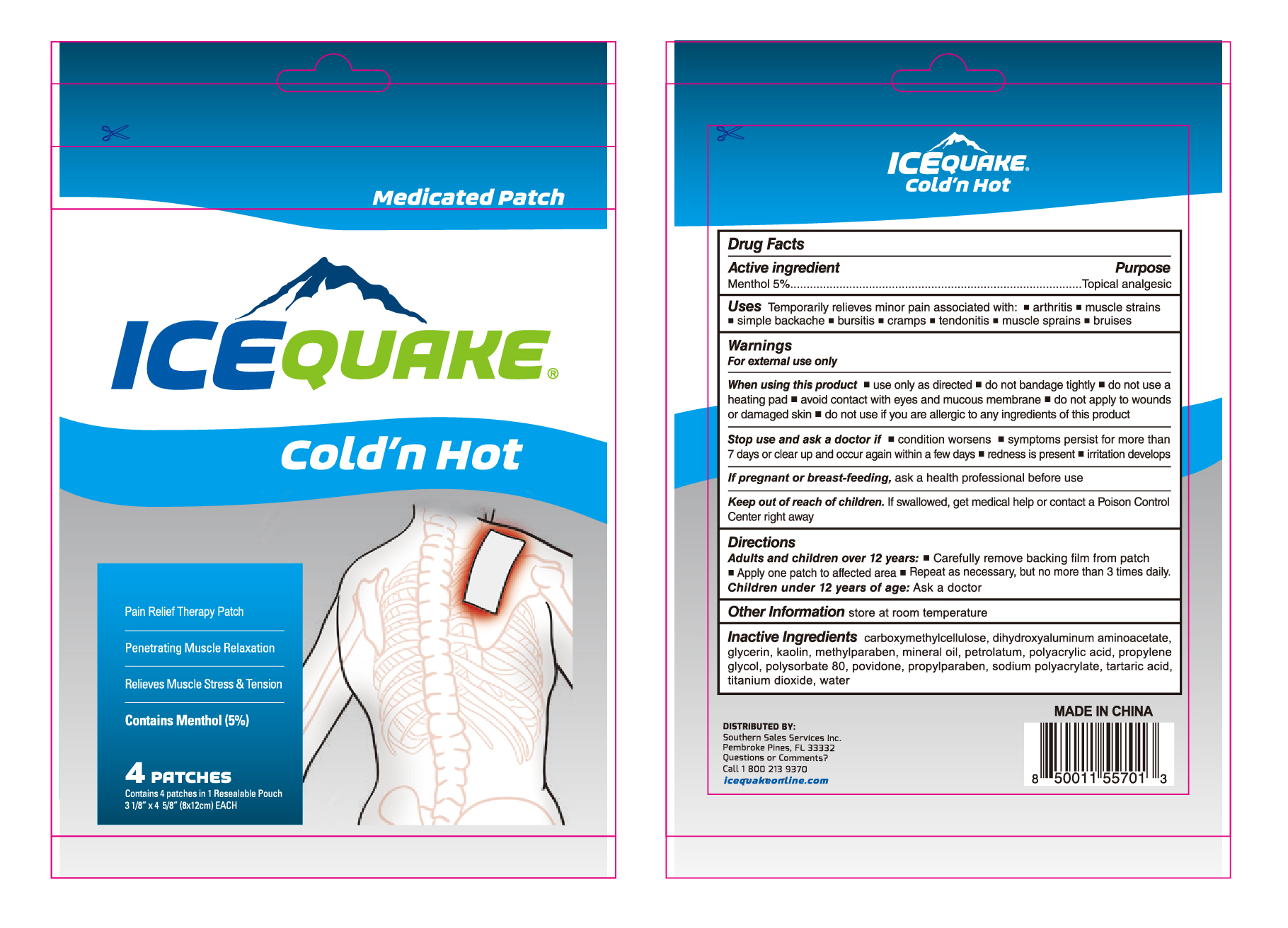 DRUG LABEL: Icequake Coldn Hot medicated patch
NDC: 69822-014 | Form: CLOTH
Manufacturer: Southern Sales & Service, Inc.
Category: otc | Type: HUMAN OTC DRUG LABEL
Date: 20231129

ACTIVE INGREDIENTS: MENTHOL 50 mg/1 g
INACTIVE INGREDIENTS: TARTARIC ACID; TITANIUM DIOXIDE; POLYSORBATE 80; CARBOXYMETHYLCELLULOSE; DIHYDROXYALUMINUM AMINOACETATE; GLYCERIN; KAOLIN; POVIDONE; METHYLPARABEN; MINERAL OIL; PETROLATUM; POLYACRYLIC ACID (250000 MW); PROPYLENE GLYCOL; WATER; PROPYLPARABEN; SODIUM POLYACRYLATE (8000 MW)

Icequake Cold'n Hot medicated patch

Active ingredient

Menthol 5%

Purpose

Topical analgesic

Uses

Temporarily relieves minor pain associated with: • arthritis • muscle strains • simple backache • bursitis • cramps • tendonitis • muscle sprains • bruises

Warnings

For external use only

When using this product

- use only as directed
- do not bandage tightly
- do not use a heating pad
- avoid contact with eyes and mucous membranes
- do not apply to wounds or damaged skin

do not use

- if you are allergic to any ingredients of this product

Stop use and ask a doctor if

- condition worsens
- symptoms persist for more than 7 days or clear up and occur again within a few days
- redness is present
- irritation develops

If pregnant or breast-feeding,

ask a health professional before use

Keep out of reach of children.

If swallowed, get medical help or conctact a Poison Control Center right away

Directions

Adults and children over 12 years:

store at room temperature Children under 12 years of age:

- Carefully remove backing film from patch
- Apply one patch to affected area
- Use one patch at a time, 1 or 2 times a day

Other Information

store at room temperature

Inactive Ingredients

CARBOXYMETHYLCELLULOSE, DIHYDROXYALUMINUM AMINOACETATE, GLYCERIN, KAOLIN, METHYLPARABEN, MINERAL OIL, PETROLATUM, POLYACRYLIC ACID , PROPYLENE GLYCOL, POLYSORBATE 80, POVIDONE, PROPYLPARABEN, SODIUM POLYACRYLATE, TARTARIC ACID, TITANIUM DIOXIDE, WATER